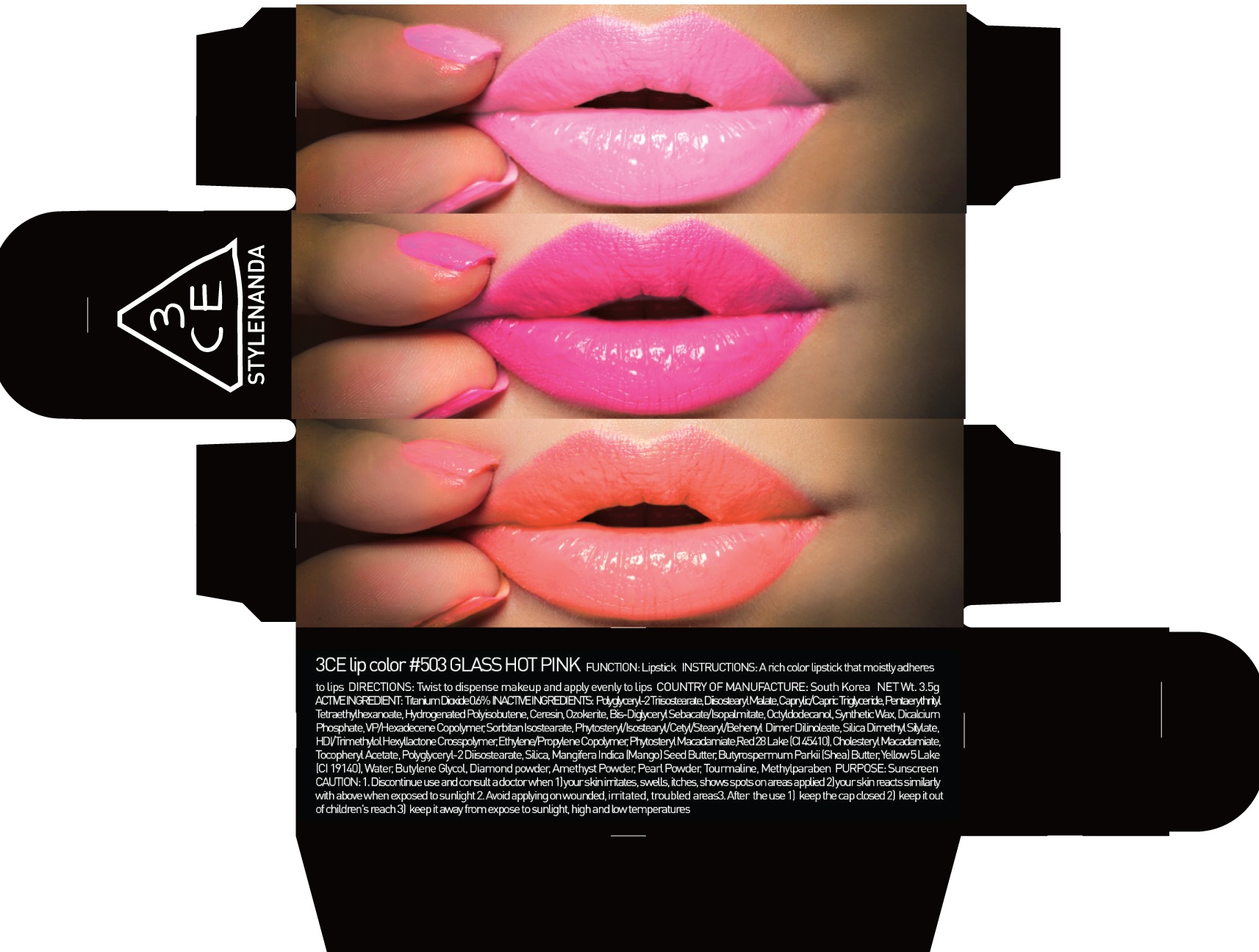 DRUG LABEL: 3CE LIP COLOR 503 GLASS HOT PINK
NDC: 60764-074 | Form: LIPSTICK
Manufacturer: Nanda Co., Ltd
Category: otc | Type: HUMAN OTC DRUG LABEL
Date: 20161007

ACTIVE INGREDIENTS: Titanium Dioxide 0.02 g/3.5 g
INACTIVE INGREDIENTS: Diisostearyl Malate; Pentaerythrityl Tetraethylhexanoate

ACTIVE INGREDIENT

Active Ingredient: Titanium Dioxide 0.6%

INACTIVE INGREDIENT

Inactive Ingredients: Polyglyceryl-2 Triisostearate, Diisostearyl Malate, Caprylic/Capric Triglyceride, Pentaerythrityl Tetraethylhexanoate, Hydrogenated Polyisobutene, Ceresin, Ozokerite, Bis-Diglyceryl Polyacyladipate-2, Diglyceryl Sebacate/Isopalmitate, Octyldodecanol, Synthetic Wax, Dicalcium Phosphate, VP/Hexadecene Copolymer, Sorbitan Isostearate, Phytosteryl/Isostearyl/Cetyl/Stearyl/Behenyl Dimer Dilinoleate, Silica Dimethyl Silylate, HDI/Trimethylol Hexyllactone Crosspolymer, Ethylene/Propylene Copolymer, Phytosteryl Macadamiate, Red 28 Lake (CI 45410), Cholesteryl Macadamiate, Tocopheryl Acetate, Polyglyceryl-2 Diisostearate, Silica, Mangifera Indica (Mango) Seed Butter, Butyrospermum Parkii (Shea) Butter, Yellow 5 Lake (CI 19140), Water, Butylene Glycol, Diamond powder, Amethyst Powder, Pearl Powder, Tourmaline, Methylparaben

PURPOSE

Purpose: Sunscreen

CAUTION

CAUTION: 1. Discontinue use and consult a doctor when - your skin irritates, swells, itches, shows spots on areas applied - your skin reacts similarly with above when exposed to sunlight 2. Avoid applying on wounded, irritated, troubled areas 3. After the use - keep the cap closed - keep it out of children's reach - keep it away from expose to sunlight, high and low temperatures

DESCRIPTION

INSTRUCTIONS: A rich color lipstick that moistly adheres to lips.

Directions: Twist to dispense makeup and apply evenly to lips